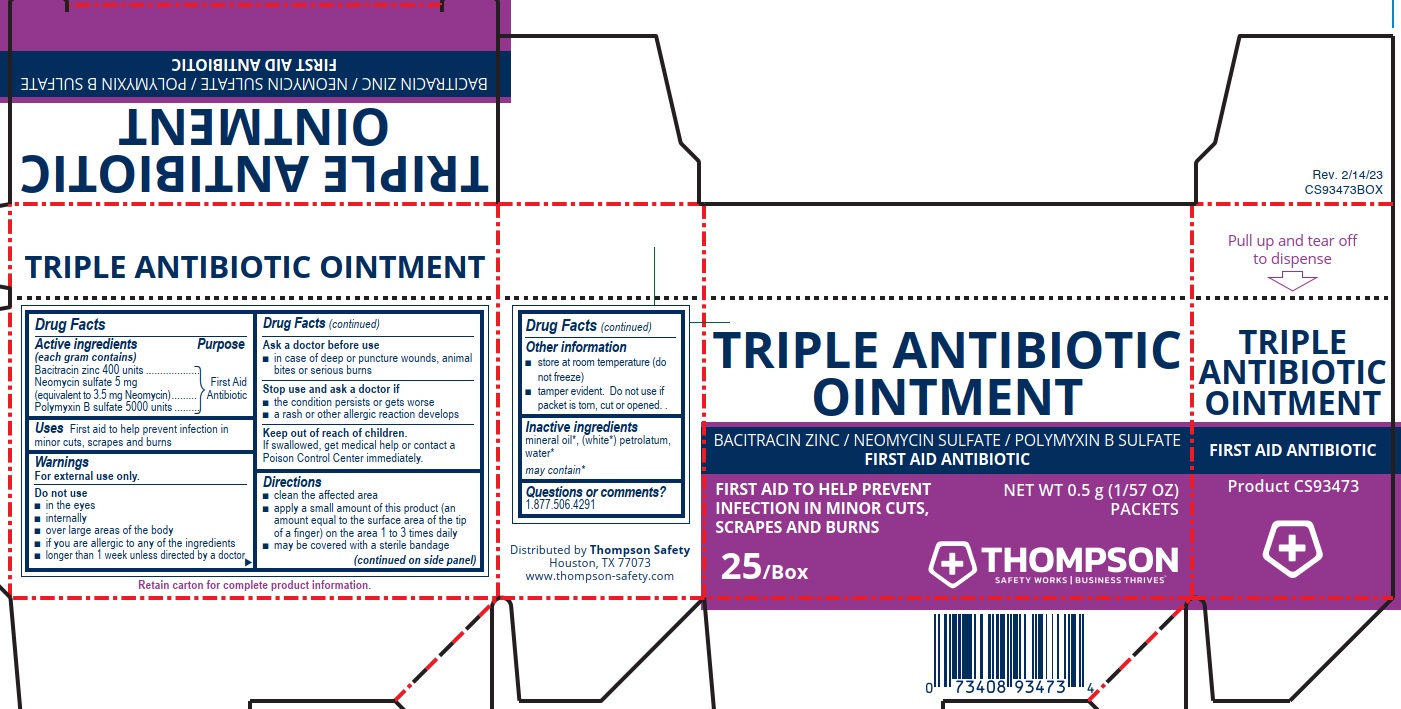 DRUG LABEL: Thompson Triple Antibiotic
NDC: 73408-983 | Form: OINTMENT
Manufacturer: Thompson
Category: otc | Type: HUMAN OTC DRUG LABEL
Date: 20250908

ACTIVE INGREDIENTS: NEOMYCIN SULFATE 3.5 mg/1 g; POLYMYXIN B SULFATE 5000 [iU]/1 g; BACITRACIN ZINC 400 [iU]/1 g
INACTIVE INGREDIENTS: WATER; MINERAL OIL; PETROLATUM

Thompson Triplle Antibiotic Ointment

Drug Facts

Active ingredient

(each gram contains)

Bacitracin zinc 400 units

Neomycin sulfate 5 mg

(equivalent to 3.5 mg Neomycin)

Polymyxin B sulfate 5000 units

Purpose

First Aid Antibiotic

First Aid Antibiotic

First Aid Antibiotic

Uses

First aid to help prevent infection in minor cuts, scrapes and burns

Warnings

For external use only.

Do not use

- in the eyes
- internally
- over large areas of the body
- if you are allergic to any of the ingredients
- longer than 1 week unless directed by a doctor

Ask a doctor before use

- in case of deep or puncture wounds, animal bites or serious burns

Stop use and ask a doctor if

- the condition persists or gets worse
- a rash or other allergic reaction develops

Keep out of reach of children.

If swallowed, get medical help or contact a Poison Control Center immediately.

Directions

- clean the affected area
- apply a small amount of this product (an amount equal to the surface area of the tip of a finger) on the area 1 to 3 times daily
- may be covered with a sterile bandage

Other information

- store at room temperature (do not freeze)
- tamper evident. Do not use if packet is torn, cut or opened.

Inactive ingredients

mineral oil*, petrolatum, water*

may contain*

Questions or comments? 1.877.506.4291

PACKAGE LABEL

Thompson Triple Antibiotic Ointment

Bacitracin Zinc / Neomycin Sulfate / Polymyxin B Sulfate

Safety Works | Business Thrives™

First Aid Antibiotic

First Aid To Help Prevent Infection In Minor Cuts, Scrapes And Burns

NET WT 0.5 g (1/57 oz) Packets

25/Box